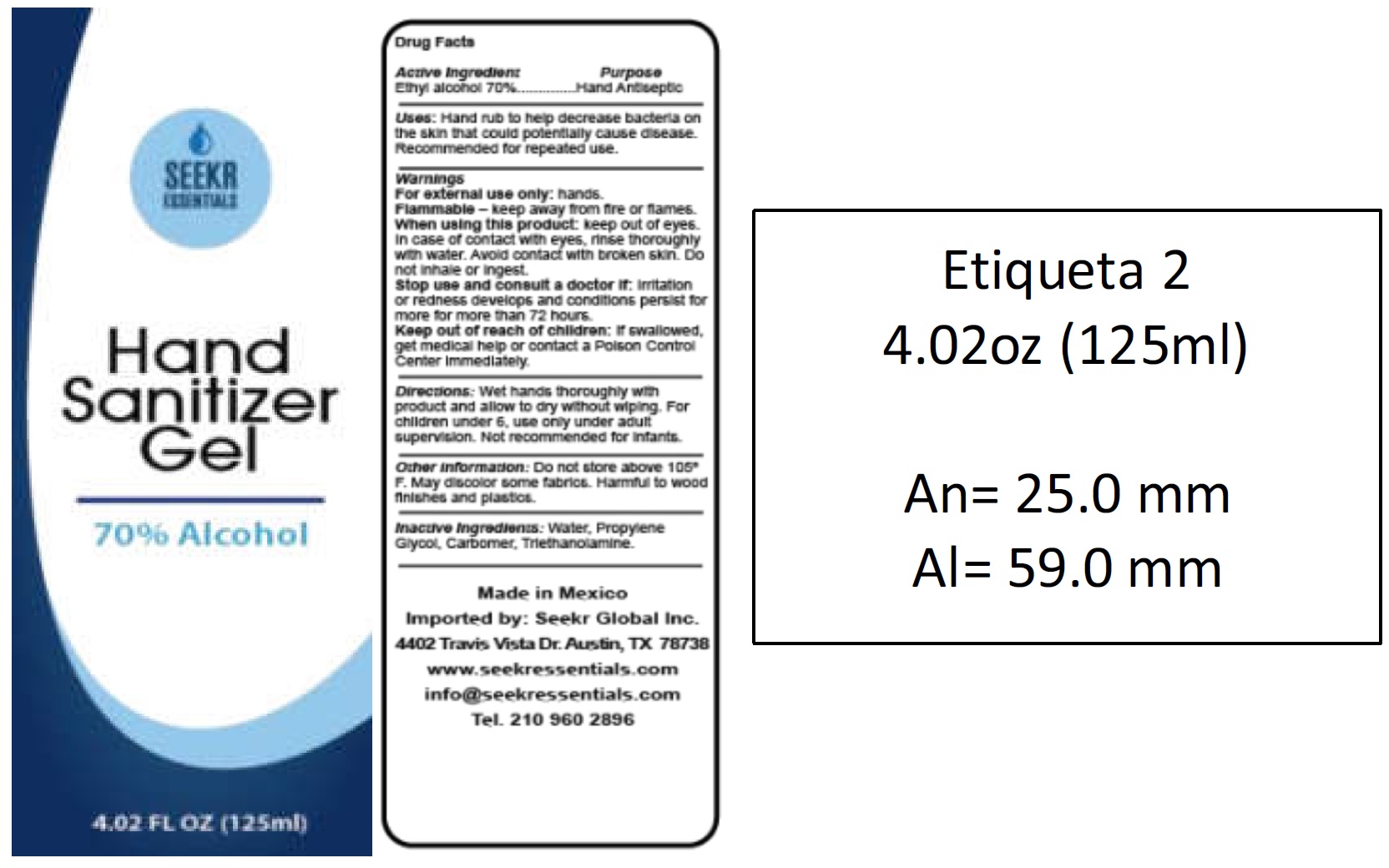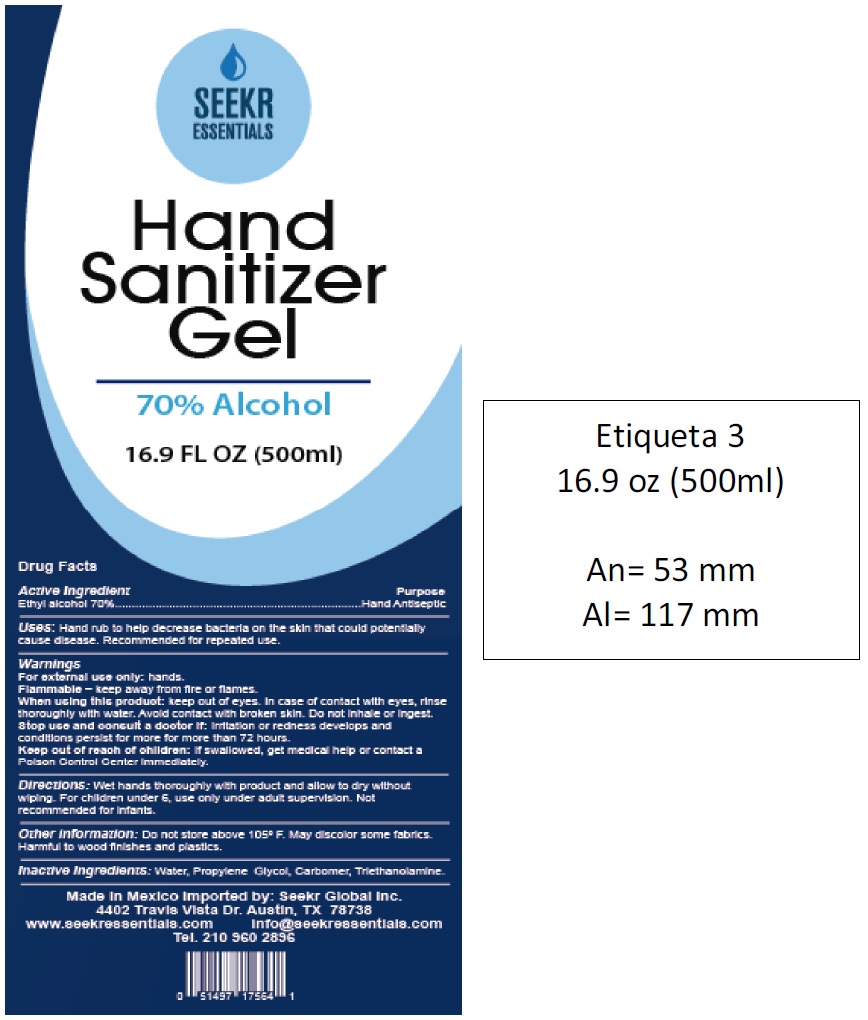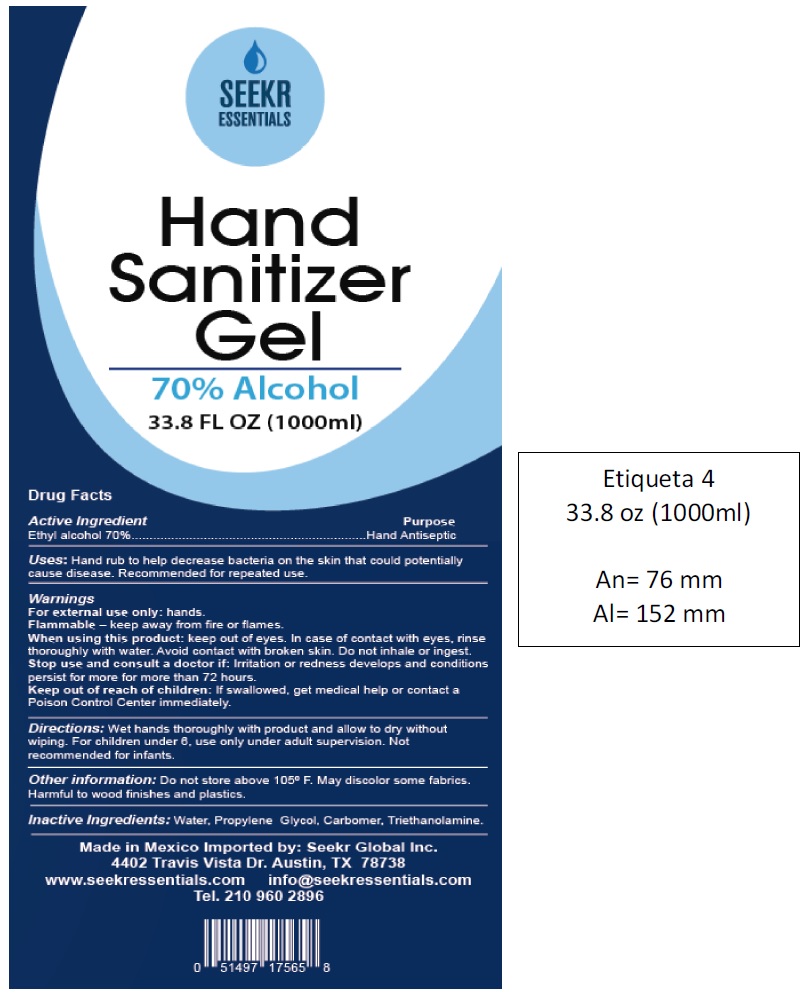 DRUG LABEL: Meni Hand Sanitizer
NDC: 79439-000 | Form: GEL
Manufacturer: Seekr Global Inc.
Category: otc | Type: HUMAN OTC DRUG LABEL
Date: 20200730

ACTIVE INGREDIENTS: ALCOHOL 0.7 mL/1 mL
INACTIVE INGREDIENTS: WATER; PROPYLENE GLYCOL; CARBOMER HOMOPOLYMER, UNSPECIFIED TYPE; TROLAMINE

Meni Hand Sanitizer Gel

Active Ingredient:

Ethyl alcohol 70%

PURPOSE

(Hand Antiseptic)

Inactive Ingredients:

Water, Propylene Glycol, Carbomer, Triethanolamine.

Directions:

Wet hands thoroughly with product and allow to dry without wiping, For children under 6, use only under adult supervision.

Use:

Health care personnel hand rub to help reduce bacteria that potentially can cause disease.

Warnings:

For external use only.

Flammable - keep away from fire or flames.

Keep ouit of reach of children.

If swallowed, get medical help or contact a Poison Control Center immediately.

Do not use

in eyes, In case of contact, rinse thoroughly with water.

Stop use and consult a doctor if

irritation or redness develops and persist for more for more than 72 hours.

Store at 20C to 25C (68F to 77F), may discolor certain fabrics.